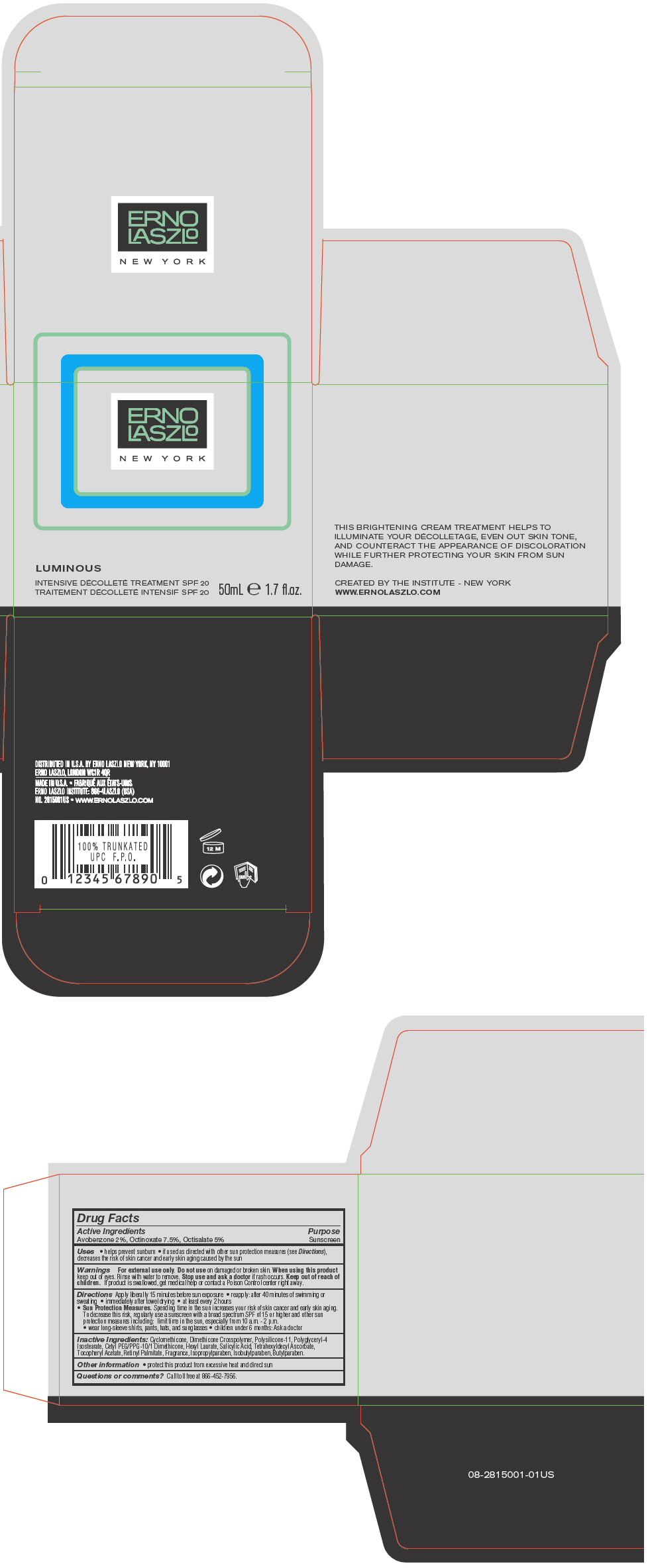 DRUG LABEL: Luminous Intensive Decollote Treatment  SPF 20
NDC: 57913-2815 | Form: LOTION
Manufacturer: Erno Laszlo, Inc.
Category: otc | Type: HUMAN OTC DRUG LABEL
Date: 20130409

ACTIVE INGREDIENTS: Avobenzone 20 mg/1 mL; Octinoxate 75 mg/1 mL; Octisalate 50 mg/1 mL
INACTIVE INGREDIENTS: Cyclomethicone; Polyglyceryl-4 Isostearate; Hexyl Laurate; Salicylic Acid; Tetrahexyldecyl Ascorbate; .Alpha.-Tocopherol Acetate; Vitamin A Palmitate; Isopropylparaben; Isobutylparaben; butylparaben

Luminous Intensive Decollote Treatment SPF 20

Drug Facts

Active Ingredients

Avobenzone 2%, Octinoxate 7.5%, Octisalate 5%

Purpose

Sunscreen

Uses

- helps prevent sunburn
- if used as directed with other sun protection measures (see Directions), decreases the risk of skin cancer and early skin aging caused by the sun

Warnings

For external use only.

Do not use on damaged or broken skin.

When using this product keep out of eyes. Rinse with water to remove.

Stop use and ask a doctor if rash occurs.

Keep out of reach of children. If product is swallowed, get medical help or contact a Poison Control center right away.

Directions

Apply liberally 15 minutes before sun exposure

- reapply: after 40 minutes of swimming or sweating
- immediately after towel drying
- at least every 2 hours
- Sun Protection Measures. Spending time in the sun increases your risk of skin cancer and early skin aging. To decrease this risk, regularly use a sunscreen with a broad spectrum SPF of 15 or higher and other sun protection measures including: limit time in the sun, especially from 10 a.m. - 2 p.m.
  - wear long-sleeve shirts, pants, hats, and sunglasses
  - children under 6 months: Ask a doctor

Inactive Ingredients

Cyclomethicone, Dimethicone Crosspolymer, Polysilicone-11, Polyglyceryl-4 Isostearate, Cetyl PEG/PPG-10/1 Dimethicone, Hexyl Laurate, Salicylic Acid, Tetrahexyldecyl Ascorbate, Tocopheryl Acetate, Retinyl Palmitate, Fragrance, Isopropylparaben, Isobutylparaben, Butylparaben.

Other information

- protect this product from excessive heat and direct sun

Questions or comments?

Call toll free at 866-452-7956.

DISTRIBUTED IN U.S.A. BY ERNO LASZLO NEW YORK, NY 10001

PRINCIPAL DISPLAY PANEL - 50 mL Jar Carton

ERNO
LASZLO

NEW YORK

LUMINOUS

INTENSIVE DÉCOLLETÉ TREATMENT SPF 20

50mL e 1.7 fl.oz.